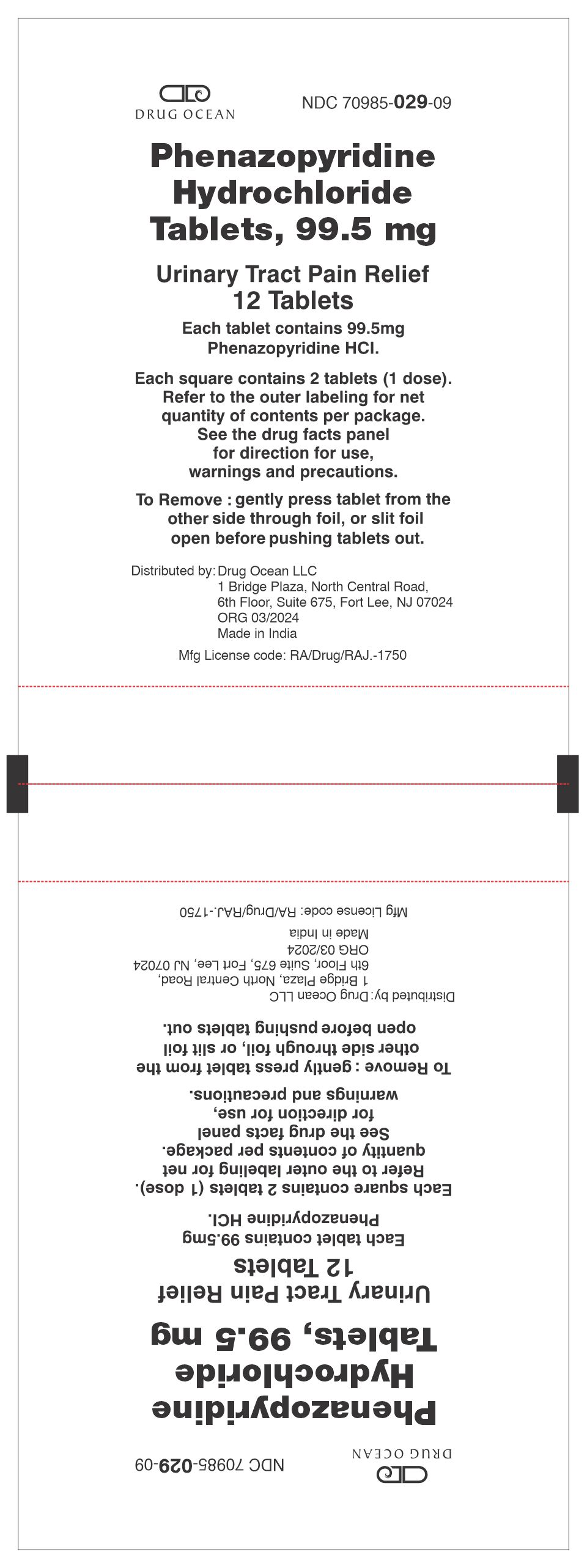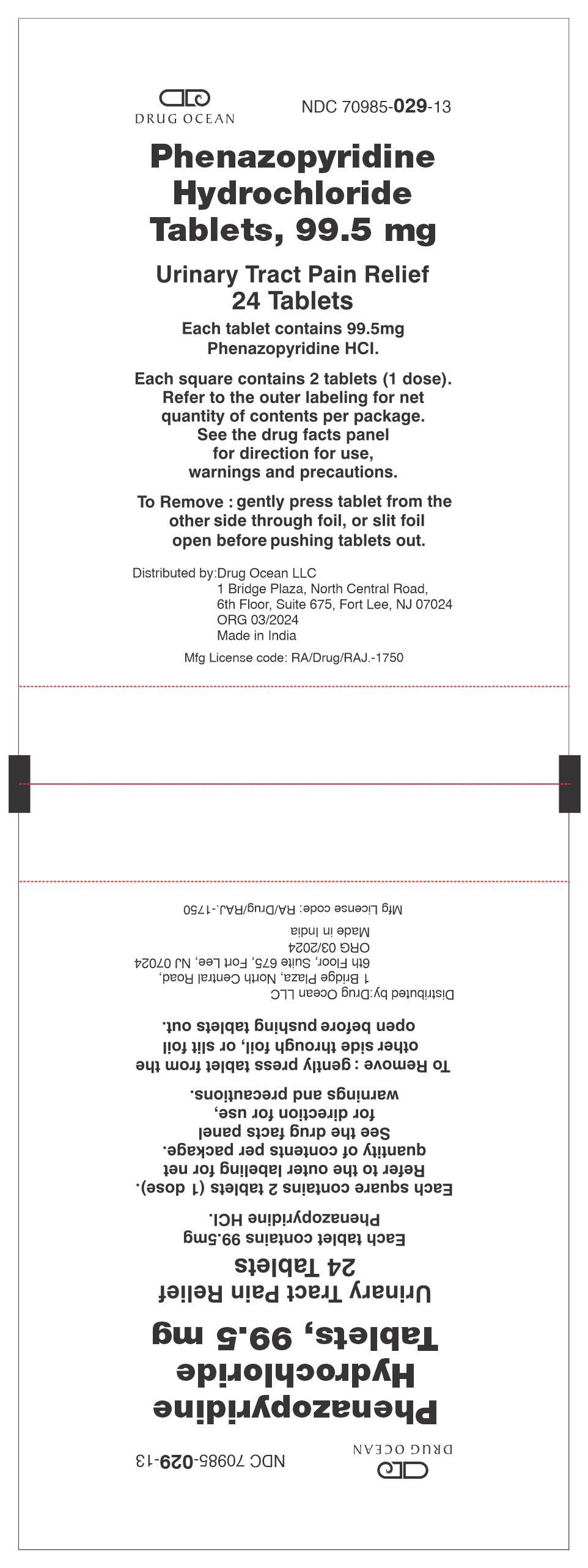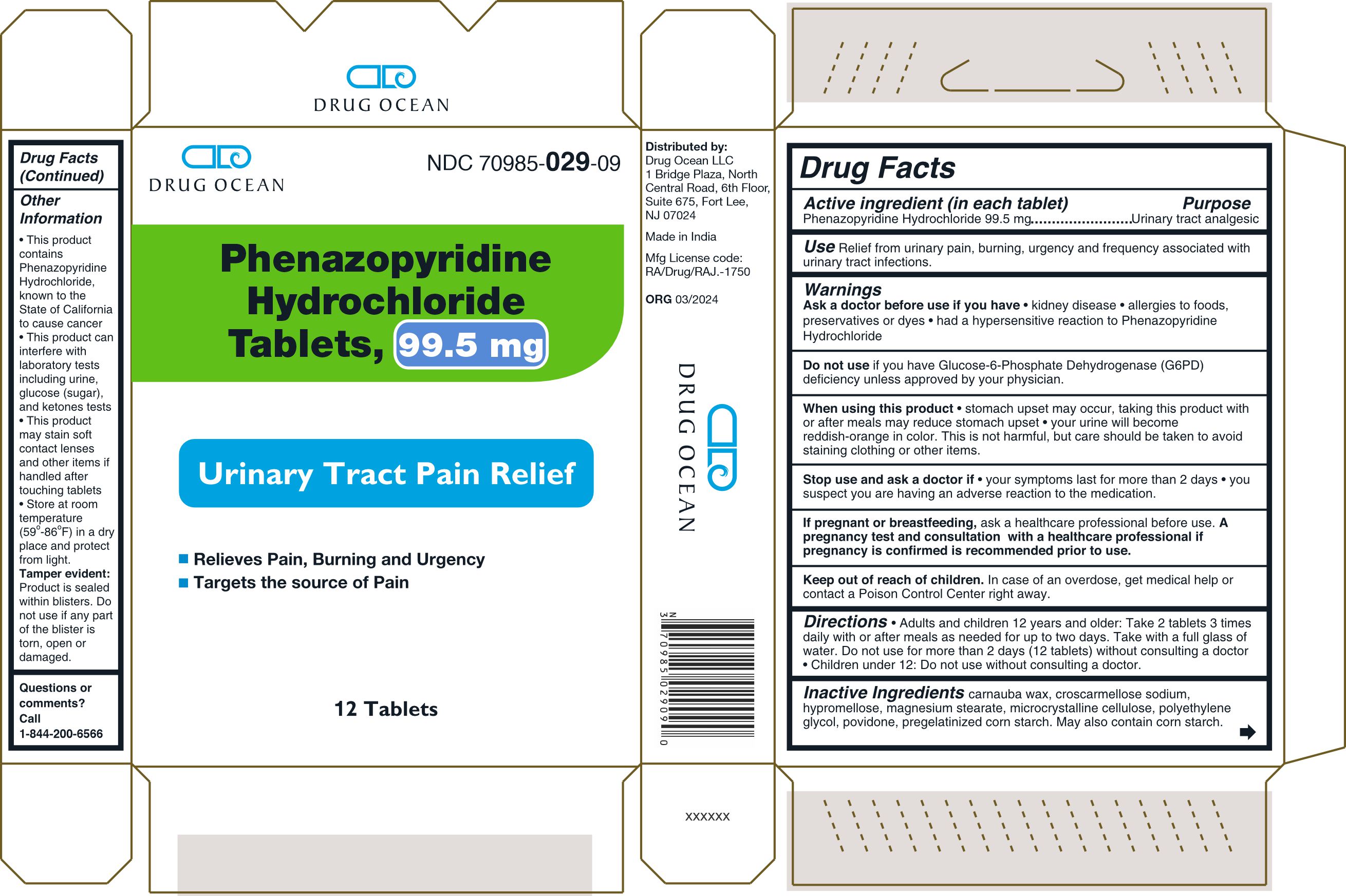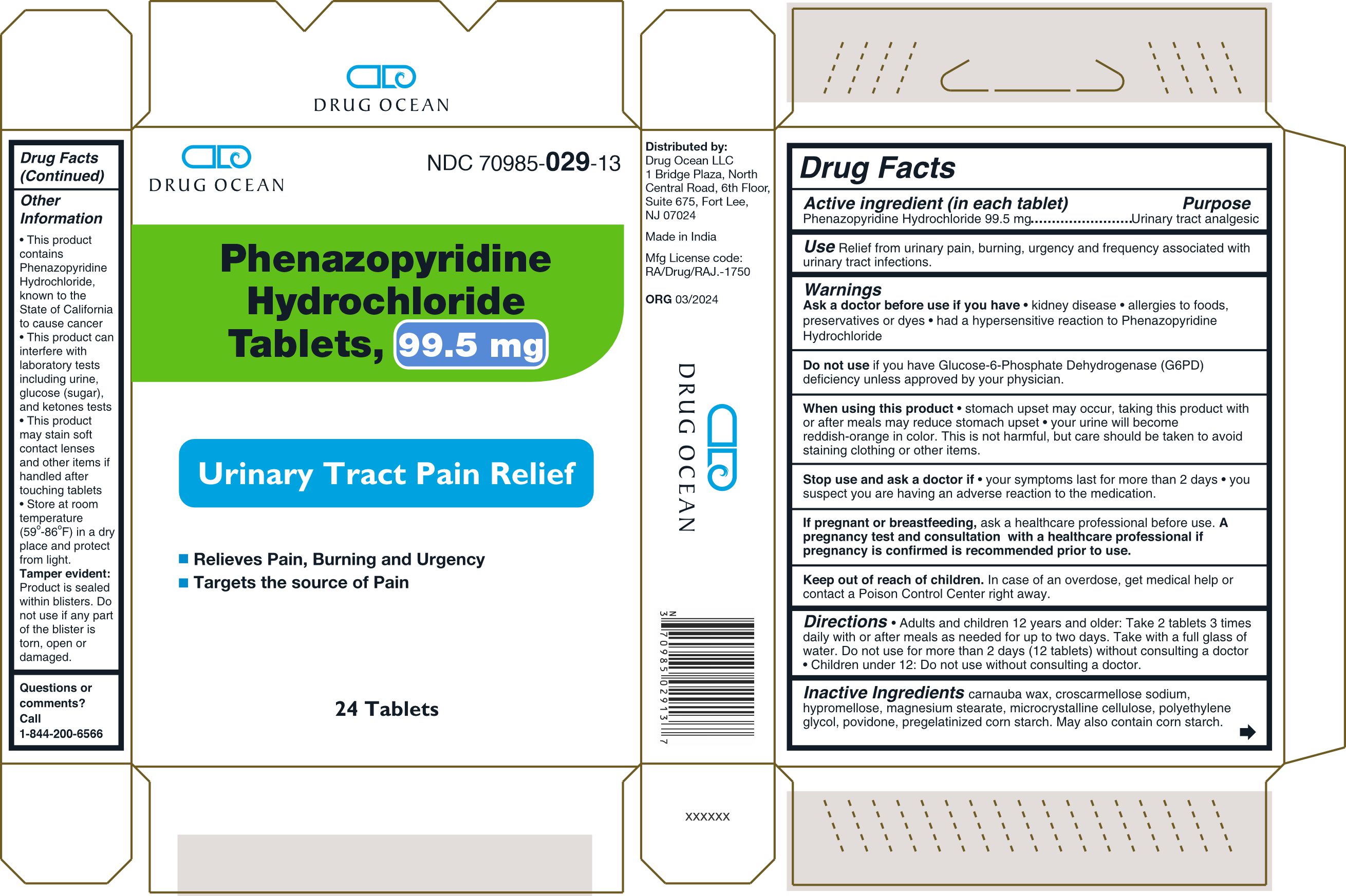 DRUG LABEL: PHENAZOPYRIDINE HYDROCHLORIDE
NDC: 70985-029 | Form: TABLET
Manufacturer: Drug Ocean LLC
Category: otc | Type: HUMAN OTC DRUG LABEL
Date: 20240327

ACTIVE INGREDIENTS: PHENAZOPYRIDINE HYDROCHLORIDE 99.5 mg/1 1
INACTIVE INGREDIENTS: MICROCRYSTALLINE CELLULOSE; STARCH, CORN; HYPROMELLOSE, UNSPECIFIED; POVIDONE, UNSPECIFIED; CROSCARMELLOSE SODIUM; POLYETHYLENE GLYCOL, UNSPECIFIED; CARNAUBA WAX; MAGNESIUM STEARATE

PHENAZOPYRIDINE HYDROCHLORIDE TABLETS

Active ingredient (in each tablet)

Phenazopyridine Hydrochloride 99.5 mg

Purpose

Urinary tract analgesic

INDICATIONS AND USAGE

UseRelief from urinary pain, burning, urgency and frequency associated with urinary tract infections.

Warnings

Ask a doctor before use if you have

- kidney disease
- allergies to foods, preservatives or dyes
- had a hypersensitive reaction to Phenazopyridine Hydrochloride

DO NOT USE

Do not useif you have Glucose-6-Phosphate Dehydrogenase (G6PD) deficiency unless approved by your physician.

When using this product

- stomach upset may occur, taking this product with or after meals may reduce stomach upset
- your urine will become reddish-orange in color. This is not harmful, but care should be taken to avoid staining clothing or other items.

Stop use and ask doctor if

- your symptoms last for more than 2 days
- you suspect you are having an adverse reaction to the medication.

PREGNANCY OR BREAST FEEDING

If pregnant or breastfeeding,ask a healthcare professional before use. A pregnancy test and consultation with a healthcare professional if pregnancy is confirmed is recommended prior to use.

Keep out of reach of children.In case of an overdose, get medical help or contact a Poison Control Center right away.

Directions

- Adults and children 12 years and older: Take 2 tablets 3 times daily with or after meals as needed for up to two days. Take with a full glass of water. Do not use for more than 2 days (12 tablets) without consulting a doctor.
- Children under 12: Do not use without consulting a doctor.

INACTIVE INGREDIENT

Inactive ingredients carnauba wax, croscarmellose sodium, hypromellose, magnesium stearate, microcrystalline cellulose, polyethylene glycol, povidone, pregelatinized corn starch. May also contain corn starch.

Other Information

- This product contains Phenazopyridine Hydrochloride, known to the State of California to cause cancer
- This product can interfere with laboratory tests including urine, glucose (sugar), and ketones tests
- This product may stain soft contact lenses and other items if handled after touching tablets
- Store at room temperature (59o-86oF) in a dry place and protect from light.

Tamper evident:Product is sealed within blisters. Do not use if any part of the blister is torn, open or damaged.

Questions or comments? Call 1-844-200-6566

Distributed by:
Drug Ocean LLC
1 Bridge Plaza, North Central Road,
6th Floor, Suite 675,
Fort Lee, NJ 07024

Made in India

Mfg License Code:
RA/Drug/RAJ.-1750

ORG 03/2024

Packaging

Drug Ocean NDC 70985- 029-09

Phenazopyridine Hydrochloride Tablets, 99.5 mg

Urinary Tract Pain Relief

- Relieves Pain, Burning and Urgency
- Targets the source of Pain

12 Tablets

Blister Label

Packaging

Drug Ocean NDC 70985- 029-13

Phenazopyridine Hydrochloride Tablets, 99.5 mg

Urinary Tract Pain Relief

- Relieves Pain, Burning and Urgency
- Targets the source of Pain

24 Tablets

Blister Label